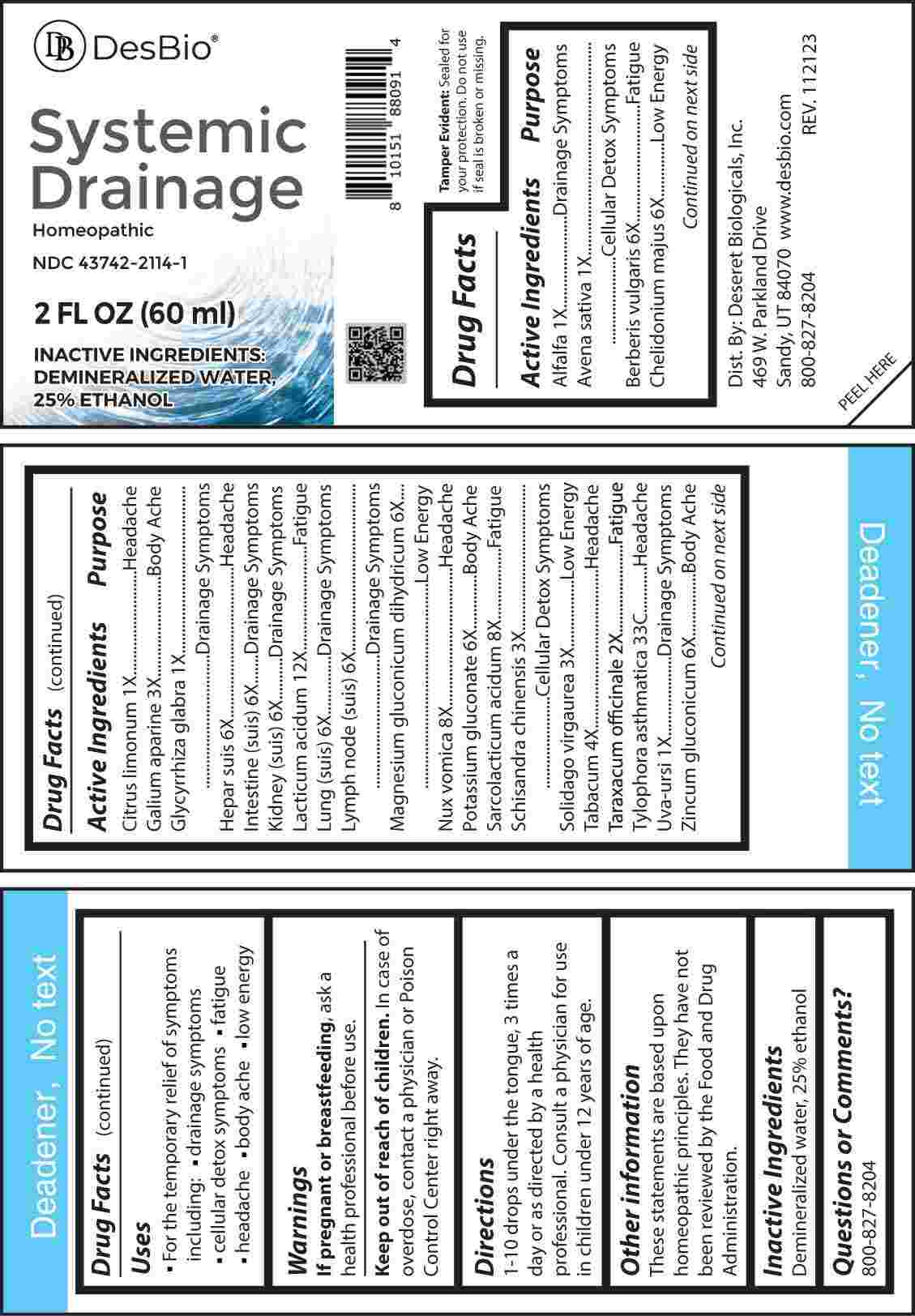 DRUG LABEL: Systemic Drainage
NDC: 43742-2114 | Form: LIQUID
Manufacturer: Deseret Biologicals, Inc.
Category: homeopathic | Type: HUMAN OTC DRUG LABEL
Date: 20240219

ACTIVE INGREDIENTS: MEDICAGO SATIVA WHOLE 1 [hp_X]/1 mL; AVENA SATIVA FLOWERING TOP 1 [hp_X]/1 mL; BERBERIS VULGARIS ROOT BARK 6 [hp_X]/1 mL; CHELIDONIUM MAJUS WHOLE 6 [hp_X]/1 mL; LEMON JUICE 1 [hp_X]/1 mL; GALIUM APARINE WHOLE 3 [hp_X]/1 mL; GLYCYRRHIZA GLABRA 1 [hp_X]/1 mL; PORK LIVER 6 [hp_X]/1 mL; PORK INTESTINE 6 [hp_X]/1 mL; PORK KIDNEY 6 [hp_X]/1 mL; LACTIC ACID, DL- 12 [hp_X]/1 mL; SUS SCROFA LUNG 6 [hp_X]/1 mL; SUS SCROFA LYMPH 6 [hp_X]/1 mL; MAGNESIUM GLUCONATE 6 [hp_X]/1 mL; STRYCHNOS NUX-VOMICA SEED 8 [hp_X]/1 mL; POTASSIUM GLUCONATE 6 [hp_X]/1 mL; LACTIC ACID, L- 8 [hp_X]/1 mL; SCHISANDRA CHINENSIS FRUIT 3 [hp_X]/1 mL; SOLIDAGO VIRGAUREA FLOWERING TOP 3 [hp_X]/1 mL; TOBACCO LEAF 4 [hp_X]/1 mL; TARAXACUM OFFICINALE 2 [hp_X]/1 mL; VINCETOXICUM INDICUM LEAF 33 [hp_C]/1 mL; VINCETOXICUM INDICUM ROOT 33 [hp_C]/1 mL; ARCTOSTAPHYLOS UVA-URSI LEAF 1 [hp_X]/1 mL; ZINC GLUCONATE 6 [hp_X]/1 mL
INACTIVE INGREDIENTS: WATER; ALCOHOL

DRUG FACTS:

ACTIVE INGREDIENTS:

Alfalfa 1X, Avena Sativa 1X, Berberis Vulgaris 6X, Chelidonium Majus 6X, Citrus Limonum 1X, Galium Aparine 3X, Glycyrrhiza Glabra 1X, Hepar Suis 6X, Intestine (Suis) 6X, Kidney (Suis) 6X, Lacticum Acidum 12X, Lung (Suis) 6X, Lymph Node (Suis) 6X, Magnesium Gluconate Dihydricum 6X, Nux Vomica 8X, Potassium Gluconate 6X, Sarcolacticum Acidum 8X, Schisandra Chinensis 3X, Solidago Virgaurea 3X, Tabacum 4X, Taraxacum Officinale 2X, Tylophora Asthmatica 33C, Uva-Ursi 1X, Zincum Gluconicum 6X.

PURPOSE:

Alfalfa – Drainage Symptoms, Avena Sativa – Cellular Detox Symptoms, Berberis Vulgaris - Fatigue, Chelidonium Majus – Low Energy, Citrus Limonum - Headache, Galium Aparine – Body Ache, Glycyrrhiza Glabra – Drainage Symptoms, Hepar Suis - Headache, Intestine (Suis) – Drainage Symptoms, Kidney (Suis) – Drainage Symptoms, Lacticum Acidum - Fatigue, Lung (Suis) – Drainage Symptoms, Lymph Node (Suis) – Drainage Symptoms, Magnesium Gluconate Dihydricum – Low Energy, Nux Vomica - Headache, Potassium Gluconate – Body Ache, Sarcolacticum Acidum - Fatigue, Schisandra Chinensis – Cellular Detox Symptoms, Solidago Virgaurea – Low Energy, Tabacum - Headache, Taraxacum Officinale - Fatigue, Tylophora Asthmatica - Headache, Uva-Ursi – Drainage Symptoms, Zincum Gluconicum – Body Ache.

USES:

• For the temporary relief of symptoms including:

• drainage symptoms • cellular detox symptoms

• Fatigue • Headache • Body Ache • Low energy

These statements are based upon homeopathic principles. They have not been reviewed by the Food and Drug Administration.

WARNINGS:

If pregnant or breast-feeding, ask a health professional before use.

Keep out of reach of children. In case of overdose, contact a physician or Poison Control Center right away.

Tamper Evident: Sealed for your protection. Do not use if seal is broken or missing.

KEEP OUT OF REACH OF CHILDREN:

In case of overdose, contact a physician or Poison Control Center right away.

DIRECTIONS:

1-10 drops under the tongue, 3 times a day or as directed by a health professional. Consult a physician for use in children under 12 years of age.

INACTIVE INGREDIENTS:

Demineralized water, 25% ethanol

QUESTIONS:

Dist. By: Deseret Biologicals, Inc.

469 W. Parkland Drive

Sandy, UT 84070

www.desbio.com

800-827-8204

PACKAGE LABEL DISPLAY:

DesBio

Systemic

Drainage

Homeopathic

NDC 43742-2114-1

2 FL OZ (60 ml)